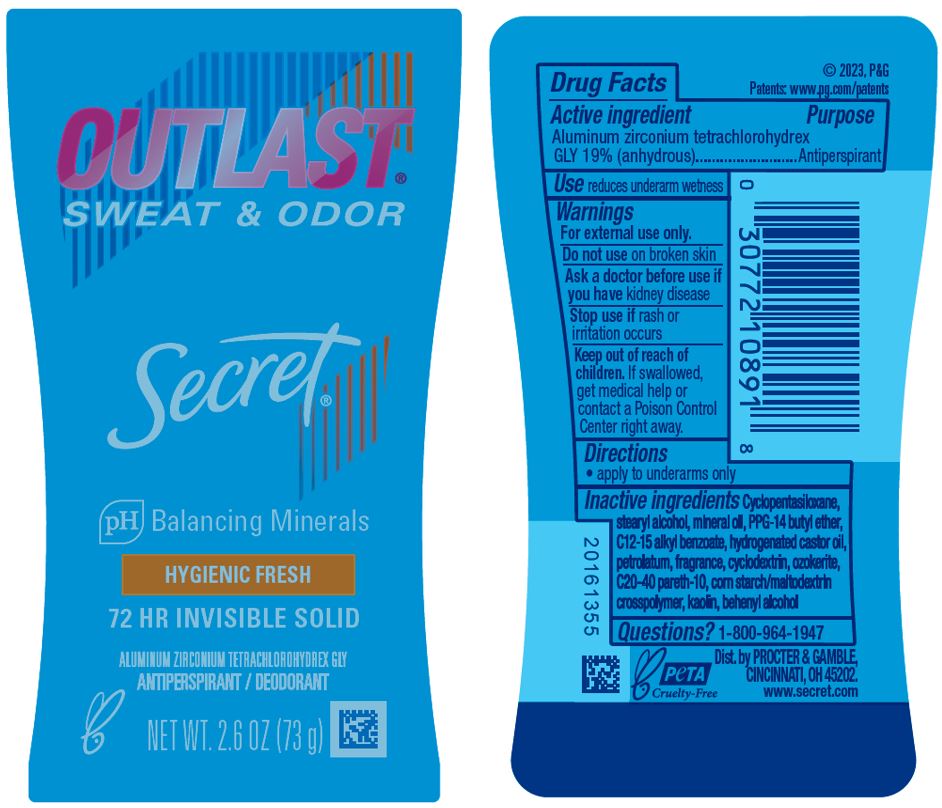 DRUG LABEL: Secret Outlast Hygienic Fresh Invisible
NDC: 69423-748 | Form: STICK
Manufacturer: The Procter & Gamble Manufacturing Company
Category: otc | Type: HUMAN OTC DRUG LABEL
Date: 20251231

ACTIVE INGREDIENTS: ALUMINUM ZIRCONIUM TETRACHLOROHYDREX GLY 19 g/100 g
INACTIVE INGREDIENTS: CYCLOMETHICONE 5; STEARYL ALCOHOL; MINERAL OIL; KAOLIN; PETROLATUM; HYDROGENATED CASTOR OIL; PPG-14 BUTYL ETHER; C20-40 PARETH-10; DOCOSANOL; BETADEX; CERESIN; ALKYL (C12-15) BENZOATE

Secret® Outlast Hygeinic Fresh Invisible

Drug Facts

Active ingredient

Aluminum zirconium tetrachlorohydrex Gly 19% (anhydrous)

Purpose

Antiperspirant

Use

reduces underarm wetness

Warnings

For external use only.

Do not use on broken skin

Ask a doctor before use if you have kidney disease

Stop use if rash or irritation occurs

Keep out of reach of children. If swallowed, get medical help or contact a Poison Control Center right away.

Directions

apply to underarms only

Inactive ingredients

Cyclopentasiloxane, stearyl alcohol, mineral oil, PPG-14 butyl ether, C12-15 alkyl benzoate, hydrogenated castor oil, petrolatum, fragrance, cyclodextrin, ozokerite, C20-40 pareth-10, corn starch/maltodextrin crosspolymer, kaolin, behenyl alcohol

Questions?

1-800-964-1947

Dist. by PROCTER & GAMBLE,
CINCINNATI, OH 45202.

PACKAGE LABEL

Secret®

OUTLAST®

pH Balancing Minerals

HYGIENIC FRESH

72 HR INVISIBLE SOLID

ALUMINUM ZIRCONIUM TETRACHLOROHYDREX GLY

ANTIPERSPIRANT / DEODORANT

NET WT. 2.6 OZ (73g)